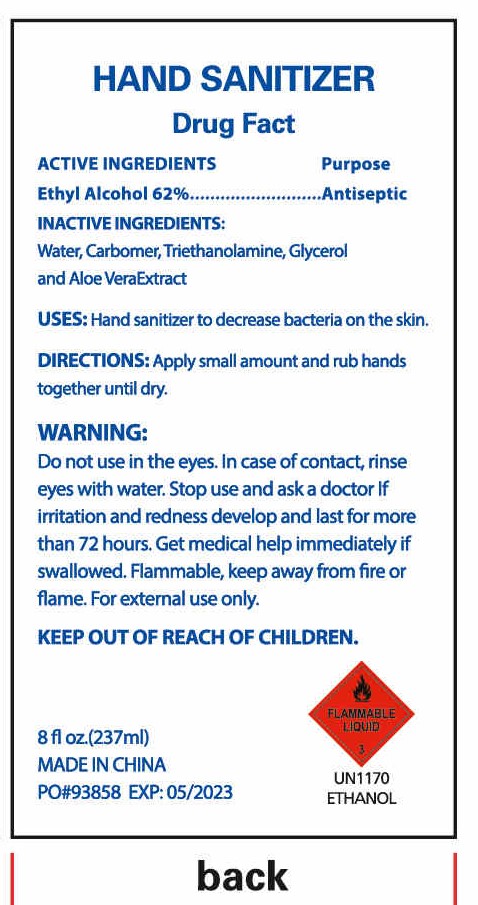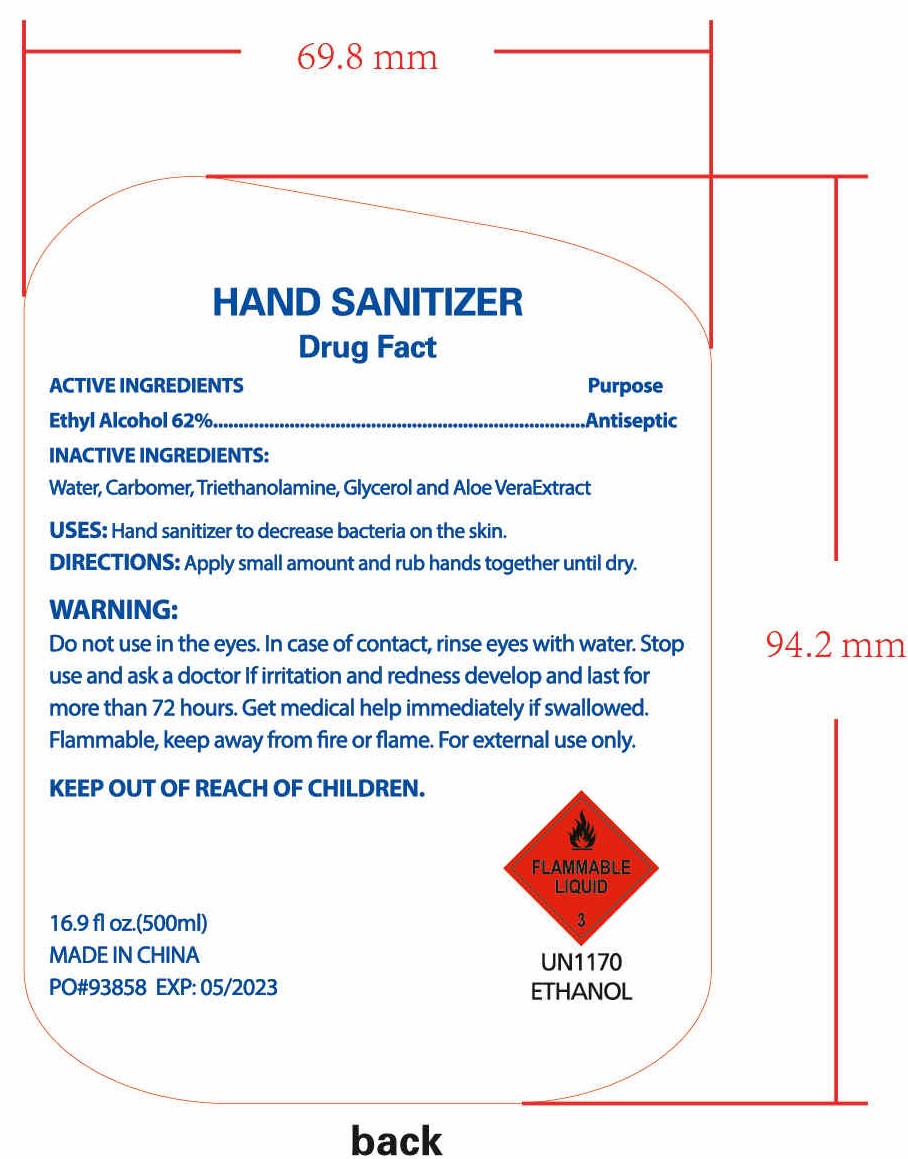 DRUG LABEL: HAND SANITIZER
NDC: 47993-261 | Form: GEL
Manufacturer: NINGBO JIANGBEI OCEAN STAR TRADING CO.,LTD
Category: otc | Type: HUMAN OTC DRUG LABEL
Date: 20201104

ACTIVE INGREDIENTS: ALCOHOL 62 g/112 mL
INACTIVE INGREDIENTS: CARBOMER 940; TRIETHANOLAMINE BENZOATE; ALOE VERA LEAF; GLYCERIN; WATER

47993-261

Active ingredients

Ethyl Alcohol 62%

Inactive Ingredients:

Water,Carbomer,Triethanolamine,Glycerol and Aloe Vera Extract.

Uses：

Hand sanitizer to decrease bacteria on the skin.

DOSAGE AND ADMINISTRATION

Apply small amount and rub hands together until dry.

Warnings:

Do not use in the eyes. In case of contact, rise eyes with water. Stop use and ask a doctor if irritation and redness develop and last for more than

72 hours. Get medical help immediately if swallowed. Flammable，keep away from fire or flame. For external use only.

Keep out of reach of children.

PURPOSE

Antiseptic